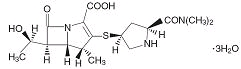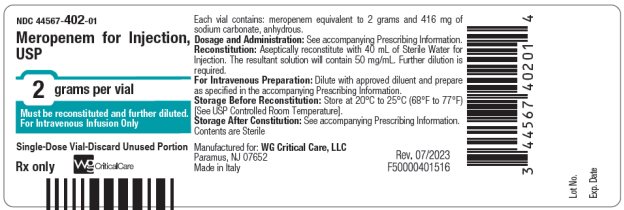 DRUG LABEL: Meropenem
NDC: 44567-402 | Form: INJECTION, POWDER, FOR SOLUTION
Manufacturer: WG Critical Care, LLC
Category: prescription | Type: HUMAN PRESCRIPTION DRUG LABEL
Date: 20260108

ACTIVE INGREDIENTS: MEROPENEM 2 g/1 1
INACTIVE INGREDIENTS: SODIUM CARBONATE 180 mg/1 1

HIGHLIGHTS OF PRESCRIBING INFORMATION

These highlights do not include all the information needed to use MEROPENEM FOR INJECTION safely and effectively. See full prescribing information for MEROPENEM FOR INJECTION.
MEROPENEM for injection, for intravenous use
Initial U.S. Approval: 1996

RECENT MAJOR CHANGES

Warnings and Precautions, Rhabdomyolysis (5.3) 12/2024

1 INDICATIONS AND USAGE

Meropenem for Injection is a penem antibacterial indicated for the treatment of bacterial meningitis in pediatric patients 3 months of age and older only. (1.1)

To reduce the development of drug-resistant bacteria and maintain the effectiveness of Meropenem for Injection and other antibacterial drugs, Meropenem for Injection should only be used to treat or prevent infections that are proven or strongly suspected to be caused by susceptible bacteria. (1.2)

2 DOSAGE AND ADMINISTRATION

- Pediatric patients 3 months of age and older with bacterial meningitis (2.1)

Recommended Meropenem for Injection Dosage Schedule for Pediatric Patients 3 Months of Age and Older with Bacterial Meningitis and Normal Renal Function (2.1)

Type of Infection

Dose (mg/kg)

Up to a Maximum Dose

Dosing Interval

Bacterial Meningitis

40

2 grams

Every 8 hours

- Intravenous infusion is to be given over approximately 15 minutes to 30 minutes.

- There is no experience with the use of Meropenem for Injection in pediatric patients with renal impairment.

3 DOSAGE FORMS AND STRENGTHS

Meropenem for Injection: 2 grams of meropenem as a powder in a single-dose vial for reconstitution (3)

4 CONTRAINDICATIONS

- Known hypersensitivity to product components or other drugs in the same class or in patients who have demonstrated anaphylactic reactions to beta (β)-lactams. (4)

5 WARNINGS AND PRECAUTIONS

- Serious and occasionally fatal hypersensitivity (anaphylactic) reactions have been reported in patients receiving β-lactams. (5.1)
- Severe cutaneous adverse reactions have been reported in patients receiving meropenem for injection. (5.2)
- Rhabdomyolysis: If signs or symptoms of rhabdomyolysis are observed, discontinue meropenem for injection and initiate appropriate therapy. (5.3)
- Seizures and other adverse CNS experiences have been reported during treatment. (5.4)
- Co-administration of meropenem for injection with valproic acid or divalproex sodium reduces the serum concentration of valproic acid potentially increasing the risk of breakthrough seizures. (5.5, 7.2)
- Clostridioides difficile-associated diarrhea (ranging from mild diarrhea to fatal colitis) has been reported. Evaluate if diarrhea occurs. (5.6)
- In patients with renal dysfunction, thrombocytopenia has been observed (5.9)

6 ADVERSE REACTIONS

Most common adverse reactions (incidence ≥ 1%) are: diarrhea, rash (mostly diaper area moniliasis), oral moniliasis, and glossitis (6.1)

To report SUSPECTED ADVERSE REACTIONS, contact WG Critical Care, LLC at 1-866-562-4708 or FDA at 1-800-FDA-1088 or www.fda.gov/medwatch.

7 DRUG INTERACTIONS

- Co-administration of meropenem for injection with probenecid inhibits renal excretion of meropenem and therefore Meropenem for Injection is not recommended (7.1)
- The concomitant use of Meropenem for Injection and valproic acid or divalproex sodium is generally not recommended. Antibacterial drugs other than carbapenems should be considered to treat infections in patients whose seizures are well controlled on valproic acid or divalproex sodium. (5.4, 7.2)

FULL PRESCRIBING INFORMATION

1 INDICATIONS AND USAGE

1.1 Bacterial Meningitis (Pediatric Patients 3 Months of Age and Older Only)

Meropenem for Injection is indicated for the treatment of bacterial meningitis caused by Haemophilus influenzae, Neisseria meningitidis andpenicillin-susceptible isolates of Streptococcus pneumoniae, in pediatric patients 3 months of age and older. Meropenem for injection has been found to be effective in eliminating concurrent bacteremia in association with bacterial meningitis.

1.2 Usage

To reduce the development of drug-resistant bacteria and maintain the effectiveness of Meropenem for Injection and other antibacterial drugs, Meropenem for Injection should only be used to treat or prevent infections that are proven or strongly suspected to be caused by susceptible bacteria. When culture and susceptibility information are available, they should be considered in selecting or modifying antibacterial therapy. In the absence of such data, local epidemiology and susceptibility patterns may contribute to the empiric selection of therapy.

2 DOSAGE AND ADMINISTRATION

2.1 Recommended Dosage in Pediatric Patients 3 Months of Age and Older with Bacterial Meningitis

- For pediatric patients 3 months of age and older with bacterial meningitis, the Meropenem for Injection recommended dosage is 40 mg/kg every 8 hours (maximum dosage is 2 grams every 8 hours).
- For pediatric patients weighing over 50 kg administer Meropenem for Injection at a dosage of 2 grams every 8 hours for bacterial meningitis.
- Administer diluted Meropenem for Injection as an intravenous infusion over approximately 15 minutes to 30 minutes [see Dosage and Administration (2.2)].
- There is limited safety data available to support the administration of a 40 mg/kg (up to a maximum of 2 grams) intravenous bolus injection. There is no experience with the use of Meropenem for Injection in pediatric patients with renal impairment [see Clinical Pharmacology (12.3)].

2.2 Preparation and Administration of Meropenem for Injection

Preparation instructions for Intravenous Infusion (Reconstitution and Dilution)

- Reconstitute Meropenem for Injection vial (2 grams) with Sterile Water for Injection according to the instructions in Table 1 below.
- Shake well to dissolve and let stand until clear.
Table 1: Volume of Sterile Water for Injection for Reconstitution of Injection Vials

Vial Size | Amount of Diluent Added (mL) | Approximate Withdrawable Volume (mL) | Approximate Average Concentration (mg/mL)
2 grams | 40 mL | 40 mL | 50 mg/mL

- Add the resulting reconstituted solution to an intravenous container and further dilute with an appropriate infusion fluid [see Dosage and Administration(2.3)and (2.4)].
- Discard unused portion.
- Parenteral drug products should be inspected visually for particulate matter and discoloration prior to administration, whenever solution and container permit. When reconstituted, the solution varies from colorless to yellow depending on the concentration.
- Do not use flexible container in series connections.

Administration Instructions for Meropenem Intravenous Infusion Solution

After reconstitution and dilution of Meropenem for Injection, administer the appropriate dose of diluted Meropenem solution as an intravenous infusion over approximately 15 minutes to 30 minutes [see Dosage and Administration (2.1)].

2.3 Compatibility

Compatibility of Meropenem for Injection with other drugs has not been established. Meropenem for Injection should not be mixed with or physically added to solutions containing other drugs.

2.4 Stability and Storage

Reconstituted Solution with Sterile Water for Injection

Use the reconstituted solution with Sterile Water for Injection immediately. However, re-constituted solutions of Meropenem for Injection maintain satisfactory potency under the conditions described below. Do not freeze reconstituted solutions of Meropenem for Injection.

Reconstituted Solution Diluted with Sodium Chloride Injection, 0.9 %

Solutions prepared for infusion (meropenem concentrations ranging from 1 mg/mL to 20 mg/mL) reconstituted with Water for Injection and further diluted with Sodium Chloride Injection 0.9% may be stored for 1 hour at up to 25°C (77°F) or 2 hours at up to 5°C (41°F).

Reconstituted Solution Diluted with Dextrose Injection, 5 %

Immediately use solutions (meropenem concentrations ranging from 1 mg/mL to 20 mg/mL) reconstituted with Water for Injection and subsequently diluted with Dextrose Injection 5%.

3 DOSAGE FORMS AND STRENGTHS

For Injection: 2 grams of meropenem as a white to light yellow powder in a single-dose vial for reconstitution.

4 CONTRAINDICATIONS

Meropenem for injection is contraindicated in patients with known hypersensitivity to any component of this product or to other drugs in the same class or in patients who have demonstrated anaphylactic reactions to beta (β)-lactams.

5 WARNINGS AND PRECAUTIONS

5.1 Hypersensitivity Reactions

Serious and occasionally fatal hypersensitivity (anaphylactic) reactions have been reported in patients receiving therapy with β-lactams. These reactions are more likely to occur in individuals with a history of sensitivity to multiple allergens.

There have been reports of individuals with a history of penicillin hypersensitivity who have experienced severe hypersensitivity reactions when treated with another β-lactam. Before initiating therapy with meropenem for injection, it is important to inquire about previous hypersensitivity reactions to penicillins, cephalosporins, other β-lactams, and other allergens. If an allergic reaction to meropenem for injection occurs, discontinue the drug immediately.

5.2 Severe Cutaneous Adverse Reactions

Severe cutaneous adverse reactions (SCAR) such as Stevens-Johnson syndrome (SJS), toxic epidermal necrolysis (TEN), drug reaction with eosinophilia and systemic symptoms (DRESS), erythema multiforme (EM) and acute generalized exanthematous pustulosis (AGEP) have been reported in patients receiving meropenem for injection [see Adverse Reactions (6.2)]. If signs and symptoms suggestive of these reactions appear, meropenem should be withdrawn immediately and an alternative treatment should be considered.

5.3 Rhabdomyolysis

Rhabdomyolysis has been reported with the use of meropenem [see Adverse Reactions (6.2)]. If signs or symptoms of rhabdomyolysis such as muscle pain, tenderness or weakness, dark urine, or elevated creatine phosphokinase are observed, discontinue meropenem for injection and initiate appropriate therapy.

5.4 Seizure Potential

Seizures and other adverse CNS experiences have been reported during treatment with meropenem for injection. These experiences have occurred most commonly in patients with CNS disorders (e.g., brain lesions or history of seizures) or with bacterial meningitis and/or compromised renal function [see Adverse Reactions(6.1) and Drug Interactions(7.2)].

During clinical investigations, 2904 immunocompetent adult patients were treated for non-CNS infections with the overall seizure rate being 0.7% (based on 20 patients with this adverse event). All meropenem-treated patients with seizures had pre-existing contributing factors. Among these included a prior history of seizures or CNS abnormality and concomitant medications with seizure potential.

Close adherence to the recommended dosage regimens is urged, especially in patients with known factors that predispose to convulsive activity. Continue anti-convulsant therapy in patients with known seizure disorders. If focal tremors, myoclonus, or seizures occur, evaluate neurologically, placed on anti-convulsant therapy if not already instituted, and re-examine the dosage of meropenem for injection to determine whether it should be decreased or discontinued.

5.5 Risk of Breakthrough Seizures Due to Drug Interaction with Valproic Acid

The concomitant use of meropenem and valproic acid or divalproex sodium is generally not recommended. Case reports in the literature have shown that co-administration of carbapenems, including meropenem, to patients receiving valproic acid or divalproex sodium results in a reduction in valproic acid concentrations. The valproic acid concentrations may drop below the therapeutic range as a result of this interaction, therefore increasing the risk of breakthrough seizures. Increasing the dose of valproic acid or divalproex sodium may not be sufficient to overcome this interaction. Consider administration of antibacterial drugs other than carbapenems to treat infections in patients whose seizures are well controlled on valproic acid or divalproex sodium. If administration of meropenem for injection is necessary, consider supplemental anti-convulsant therapy [see Drug Interactions (7.2)].

5.6 Clostridioides difficile–associated Diarrhea

Clostridioides difficile-associated diarrhea (CDAD) has been reported with use of nearly all antibacterial agents, including meropenem for injection, and may range in severity from mild diarrhea to fatal colitis. Treatment with antibacterial agents alters the normal flora of the colon leading to overgrowth of C. difficile.

C. difficile produces toxins A and B which contribute to the development of CDAD. Hypertoxin producing isolates of C. difficile cause increased morbidity and mortality, as these infections can be refractory to antimicrobial therapy and may require colectomy. CDAD must be considered in all patients who present with diarrhea following antibacterial drug use. Careful medical history is necessary since CDAD has been reported to occur over two months after the administration of antibacterial agents.

If CDAD is suspected or confirmed, ongoing antibacterial drug use not directed against C. difficile may need to be discontinued. Appropriate fluid and electrolyte management, protein supplementation, antibacterial drug treatment of C. difficile, and surgical evaluation should be instituted as clinically indicated.

5.7 Development of Drug-Resistant Bacteria

Prescribing meropenem for injection in the absence of a proven or strongly suspected bacterial infection or a prophylactic indication is unlikely to provide benefit to the patient and increases the risk of the development of drug-resistant bacteria.

5.8 Overgrowth of Nonsusceptible Organisms

As with other broad-spectrum antibacterial drugs, prolonged use of meropenem may result in overgrowth of nonsusceptible organisms. Repeated evaluation of the patient is essential. If superinfection does occur during therapy, appropriate measures should be taken.

5.9 Thrombocytopenia

In patients with renal impairment, thrombocytopenia has been observed but no clinical bleeding reported [see Dosage and Administration (2.2), Adverse Reactions (6.1), and Clinical Pharmacology (12.3)].

5.10 Potential for Neuromotor Impairment

Alert patients receiving meropenem for injection on an outpatient basis regarding adverse events such as seizures, delirium, headaches and/or paresthesias that could interfere with mental alertness and/or cause motor impairment. Until it is reasonably well established that meropenem for injection is well tolerated, advise patients not to operate machinery or motorized vehicles [see Adverse Reactions (6.1)].

6 ADVERSE REACTIONS

The following are discussed in greater detail in other sections of labeling:

- Hypersensitivity Reactions [see Warnings and Precautions (5.1)]
- Severe Cutaneous Adverse Reactions [see Warnings and Precautions (5.2)]
- Rhabdomyolysis [see Warnings and Precautions (5.3)]
- Seizure Potential [see Warnings and Precautions (5.4)]
- Risk of Breakthrough Seizures Due to Drug Interaction with Valproic Acid [see Warnings and Precautions (5.5)]
- Clostridioides difficile – Associated Diarrhea [see Warnings and Precautions (5.6)]
- Development of Drug-Resistant Bacteria [see Warnings and Precautions (5.7)]
- Overgrowth of Nonsusceptible Organisms [see Warnings and Precautions (5.8)]
- Thrombocytopenia [see Warnings and Precautions (5.9)]
- Potential for Neuromotor Impairment [see Warnings and Precautions (5.10)]

6.1 Clinical Trials Experience

Because clinical trials are conducted under widely varying conditions, adverse reactions rates observed in the clinical trials of a drug cannot be directly compared to rates in the clinical trials of another drug and may not reflect the rates observed in practice.

Adverse Reactions in Pediatric Patients with Bacterial Meningitis

Meropenem for injection was studied in 321 pediatric patients (3 months to less than 17 years of age) with bacterial meningitis at a dosage of 40 mg/kg every 8 hours. The most common adverse reactions and their rates of occurrence were as follows:

Diarrhea 4.7%
Rash (mostly diaper area moniliasis) 3.1%
Oral Moniliasis 1.9%
Glossitis 1%

In these studies, the rates of seizure activity during therapy were comparable between patients with no CNS abnormalities who received meropenem for injection and those who received comparator agents (either cefotaxime or ceftriaxone). In the meropenem for injection-treated group, 12/15 patients with seizures had late onset seizures (seizures that occurred on day 3 or later) versus 7/20 patients in the comparator arm.

The meropenem for injection group had a statistically higher number of patients than the comparator with transient elevation of liver enzymes.

Adverse Reactions from Studies of Meropenem for Injectionin Other Serious Bacterial Infections (not bacterial meningitis)

The following adverse reactions occurred in studies of 2,904 immunocompetent adult patients who received meropenem for injection (500 mg or 1 gram every 8 hours) for the treatment of other serious bacterial infections (not bacterial meningitis). This meropenem for injection product is indicated only for the treatment of bacterial meningitis caused by certain organisms in pediatric patients 3 months of age and older [see Indications and Usage (1.1)]. Many patients in these studies were severely ill and had multiple background diseases, physiological impairments and were receiving multiple other drug therapies. In the seriously ill patient population, it was not possible to determine the relationship between observed adverse events and therapy with meropenem for injection.

Deaths in 5 patients were assessed as possibly related to meropenem for injection; 36 (1.2%) patients had meropenem for injection discontinued because of adverse events.

Local Adverse Reactions

Local adverse reactions that were reported with meropenem for injection were as follows: Inflammation at the injection site (2.4%), injection site reaction (0.9%), phlebitis/thrombophlebitis (0.8%), pain at the injection site (0.4%), and edema at the injection site (0.2%)

Systemic Adverse Reactions

Systemic adverse reactions that occurred in greater than 1% of the meropenem for injection-treated patients were diarrhea (4.8%), nausea/vomiting (3.6%), headache (2.3%), rash (1.9%), sepsis (1.6%), constipation (1.4%), apnea (1.3%), shock (1.2%), and pruritus (1.2%). Additional systemic adverse reactions that occurred in less than or equal to 1% but greater than 0.1% of the meropenem for injection-treated patients are listed below within each body system in order of decreasing frequency:

Bleeding Events: gastrointestinal hemorrhage (0.5%), melena (0.3%), epistaxis (0.2%), hemoperitoneum (0.2%).

Body as a Whole: pain, abdominal pain, chest pain, fever, back pain, abdominal enlargement, chills, pelvic pain

Cardiovascular: heart failure, heart arrest, tachycardia, hypertension, myocardial infarction, pulmonary embolus, bradycardia, hypotension, syncope

Digestive System: oral moniliasis, anorexia, cholestatic jaundice/jaundice, flatulence, ileus, hepatic failure, dyspepsia, intestinal obstruction

Hemic/Lymphatic: anemia, hypochromic anemia, hypervolemia

Metabolic/Nutritional: peripheral edema, hypoxia

Nervous System: insomnia, agitation, delirium, confusion, dizziness, seizure, nervousness, paresthesia, hallucinations, somnolence, anxiety, depression, asthenia

Respiratory: respiratory disorder, dyspnea, pleural effusion, asthma, cough increased, lung edema

Skin and Appendages: urticaria, sweating, skin ulcer

Urogenital System: dysuria, kidney failure, vaginal moniliasis, urinary incontinence

Laboratory Abnormalities

Laboratory abnormalities that occurred in greater than 0.2% of the meropenem for injection-treated patients were as follows:

Hepatic: increased alanine transaminase (ALT), aspartate transaminase (AST), alkaline phosphatase, lactate dehydrogenase (LDH), and bilirubin

Hematologic: increased platelets, increased eosinophils, decreased platelets, decreased hemoglobin, decreased hematocrit, decreased white blood cell (WBC), shortened prothrombin time and shortened partial thromboplastin time, leukocytosis, hypokalemia

Renal: increased creatinine and increased blood urea nitrogen (BUN)

Urinalysis: presence of red blood cells

6.2 Post-marketing Experience

The following adverse reactions have been identified during post-approval use of meropenem, including meropenem for injection. Because these reactions are reported voluntarily from a population of uncertain size, it is not always possible to reliably estimate their frequency or establish a causal relationship to drug exposure.

Worldwide post-marketing adverse reactions not otherwise listed under the Clinical Trials Experience subsection [see Adverse Reactions (6.1)] and reported as possibly, probably, or definitely drug related are listed within each body system in order of decreasing severity.

Blood and Lymphatic System Disorders: agranulocytosis, neutropenia, and leukopenia; a positive direct or indirect Coombs test, and hemolytic anemia.

Immune System Disorders: angioedema

Skin and Subcutaneous Disorders: Stevens-Johnson syndrome, toxic epidermal necrolysis, drug reaction with eosinophilia and systemic symptoms (DRESS), erythema multiforme and acute generalized exanthematous pustulosis.

Musculoskeletal Disorders: rhabdomyolysis

7 DRUG INTERACTIONS

7.1 Probenecid

Probenecid competes with meropenem for active tubular secretion, resulting in increased plasma concentrations of meropenem. Co-administration of probenecid with meropenem is not recommended.

7.2 Valproic Acid

Case reports in the literature have shown that co-administration of carbapenems, including meropenem, to patients receiving valproic acid or divalproex sodium results in a reduction in valproic acid concentrations. The valproic acid concentrations may drop below the therapeutic range as a result of this interaction, therefore increasing the risk of breakthrough seizures. Although the mechanism of this interaction is unknown, data from in vitro and animal studies suggest that carbapenems may inhibit the hydrolysis of valproic acid’s glucuronide metabolite (VPA-g) back to valproic acid, thus decreasing the serum concentrations of valproic acid. If administration of meropenem for injection is necessary, then supplemental anti-convulsant therapy should be considered [see Warnings and Precautions(5.4)].

8 USE IN SPECIFIC POPULATIONS

8.1 Pregnancy

Risk Summary

There are insufficient human data to establish whether there is a drug-associated risk of major birth defects or miscarriages with meropenem in pregnant women.

No fetal toxicity or malformations were observed in pregnant rats and Cynomolgus monkeys administered intravenous meropenem during organogenesis at doses up to 2.4 and 2.3 times the maximum recommended human dose (MRHD) based on body surface area comparison, respectively. In rats administered intravenous meropenem in late pregnancy and during the lactation period, there were no adverse effects on offspring at doses equivalent to approximately 3.2 times the MRHD based on body surface area comparison (see Data).

The background risk of major birth defects and miscarriage for the indicated population is unknown. All pregnancies have a background risk of birth defect, loss, or other adverse outcomes. In the U.S. general population, the estimated background risk of major birth defects and miscarriage in clinically recognized pregnancies is 2% to 4% and 15% to 20%, respectively.

Data

Meropenem administered to pregnant rats during organogenesis (Gestation Day 6 to Gestation Day 17) in intravenous doses of 240, 500, and 750 mg/kg/day was associated with mild maternal weight loss at all doses, but did not produce malformations or fetal toxicity. The no-observed-adverse-effect-level (NOAEL) for fetal toxicity in this study was considered to be the high dose of 750 mg/kg/day (equivalent to approximately 2.4 times the MRHD of 1 gram every 8 hours based on body surface area comparison). Meropenem administered intravenously to pregnant Cynomolgus monkeys during organogenesis from Day 20 to 50 after mating at doses of 120, 240, and 360 mg/kg/day did not produce maternal or fetal toxicity at the NOAEL dose of 360 mg/kg/day (approximately 2.3 times the MRHD based on body surface area comparison).

In a peri-postnatal study in rats described in the published literature^1, intravenous meropenem was administered to dams from Gestation Day 17 until Lactation Day 21 at doses of 240, 500, and 1000 mg/kg/day. There were no adverse effects in the dams and no adverse effects in the first generation offspring (including developmental, behavioral, and functional assessments and reproductive parameters) except that female offspring exhibited lowered body weights which continued during gestation and nursing of the second generation offspring. Second generation offspring showed no meropenem-related effects. The NOAEL value was considered to be 1000 mg/kg/day (approximately 3.2 times the MRHD based on body surface area comparisons).

8.2 Lactation

Risk Summary

Meropenem has been reported to be excreted in human milk. No information is available on the effects of meropenem on the breast-fed child or on milk production. The developmental and health benefits of breastfeeding should be considered along with the mother’s clinical need for meropenem for injection and any potential adverse effects on the breast-fed child from meropenem for injection or from the underlying maternal conditions.

8.4 Pediatric Use

The safety and effectiveness of Meropenem for Injection have been established for pediatric patients 3 months of age and older for the treatment of bacterial meningitis caused by Haemophilus influenzae, Neisseria meningitidis and penicillin-susceptible isolates of Streptococcus pneumoniae, and the information on this use is discussed throughout the labeling.

The safety and effectiveness of Meropenem for Injection have not been established in pediatric patients younger than 3 months of age.

10 OVERDOSAGE

In mice and rats, large intravenous doses of meropenem (2200 mg/kg to 4000 mg/kg) have been associated with ataxia, dyspnea, convulsions, and mortalities.

Intentional overdosing of meropenem for injection is unlikely, although accidental overdosing might occur if large doses are given to patients with reduced renal function. The largest dose of meropenem administered in clinical trials has been 2 grams given intravenously every 8 hours. At this dosage, no adverse pharmacological effects or increased safety risks have been observed.

Limited postmarketing experience indicates that if adverse events occur following overdosage, they are consistent with the adverse event profile described in the Adverse Reactions section and are generally mild in severity and resolve on withdrawal or dose reduction. Consider symptomatic treatments. In individuals with normal renal function, rapid renal elimination takes place. Meropenem and its metabolite are readily dialyzable and effectively removed by hemodialysis; however, no information is available on the use of hemodialysis to treat overdosage.

11 DESCRIPTION

Meropenem for Injection contains meropenem a synthetic carbapenem antibacterial. Meropenem is (4R,5S,6S)-3-[[(3S,5S)-5-(Dimethylcarbamoyl)-3-pyrrolidinyl]thio]-6-[(1R)-1-hydroxyethyl]-4-methyl-7-oxo-1-azabicyclo[3.2.0]hept-2-ene-2-carboxylic acid trihydrate. Its empirical formula is C17H25N3O5S•3H2O with a molecular weight of 437.52. Its structural formula is:

Meropenem is soluble in 5% monobasic potassium phosphate solution, sparingly soluble in water, very slightly soluble in hydrated ethanol, and practically insoluble in acetone or ether.

Meropenem for Injection is a white to pale yellow sterile powder for intravenous administration. Each vial contains meropenem equivalent to 2 grams and 416 mg of sodium bicarbonate, anhydrous. When re-constituted as instructed Meropenem for Injection will deliver 2 grams of meropenem (on anhydrous basis) and approximately 180 mg of sodium as sodium carbonate (7.8 mEq) [see Dosage and Administration (2.2)]. The solution varies from colorless to yellow depending on the concentration. The pH of freshly constituted solutions is between 7.3 and 8.3.

12 CLINICAL PHARMACOLOGY

12.1 Mechanism of Action

Meropenem is an antibacterial drug [see Microbiology (12.4)].

12.2 Pharmacodynamics

The percentage of time of a dosing interval that unbound plasma concentration of meropenem exceeds the meropenem minimum inhibitory concentration (MIC) against the infecting organism has been shown to best correlate with efficacy in animal and in vitro models of infection.

12.3 Pharmacokinetics

Plasma Concentrations

At the end of a 30-minute intravenous infusion of a single dose of meropenem for injection in healthy volunteers, mean peak plasma concentrations of meropenem are approximately 49 mcg/mL (range 39 to 58) for the 1 gram dose.

Following intravenous doses of 500 mg, mean plasma concentrations of meropenem usually decline to approximately 1 mcg/mL at 6 hours after administration.

No accumulation of meropenem in plasma was observed with regimens using 1 gram administered every 6 hours in healthy volunteers with normal renal function.

Distribution

The plasma protein binding of meropenem is approximately 2%.

After a single intravenous dose of meropenem for injection, the highest mean concentrations of meropenem were found in tissues and fluids at 1 hour (0.5 hours to 1.5 hours) after the start of infusion, except where indicated in the tissues and fluids listed in Table 2 below.

Table 1: Meropenem Concentrations in Selected Tissues (Highest Concentrations Reported)
Tissue | Intravenous Dose; (gram) | Number of Samples | Mean [mcg/mL; or mcg/(gram)] [at 1 hour unless otherwise noted] | Range [mcg/mL or; mcg/(gram)]
Endometrium | 0.5 | 7 | 4.2 | 1.7 to 10.2
Myometrium | 0.5 | 15 | 3.8 | 0.4 to 8.1
Ovary | 0.5 | 8 | 2.8 | 0.8 to 4.8
Cervix | 0.5 | 2 | 7 | 5.4 to 8.5
Fallopian tube | 0.5 | 9 | 1.7 | 0.3 to 3.4
Skin | 0.5 | 22 | 3.3 | 0.5 to 12.6
Interstitial fluid [obtained from blister fluid] | 0.5 | 9 | 5.5 | 3.2 to 8.6
Skin | 1 | 10 | 5.3 | 1.3 to 16.7
Interstitial fluid | 1 | 5 | 26.3 | 20.9 to 37.4
Colon | 1 | 2 | 2.6 | 2.5 to 2.7
Bile | 1 | 7 | 14.6 (3 hours) | 4 to 25.7
Gall bladder | 1 | 1 | - | 3.9
Peritoneal fluid | 1 | 9 | 30.2 | 7.4 to 54.6
Lung | 1 | 2 | 4.8 (2 hours) | 1.4 to 8.2
Bronchial mucosa | 1 | 7 | 4.5 | 1.3 to 11.1
Muscle | 1 | 2 | 6. 1 (2 hours) | 5.3 to 6.9
Fascia | 1 | 9 | 8.8 | 1.5 to 20
Heart valves | 1 | 7 | 9.7 | 6.4 to 12.1
Myocardium | 1 | 10 | 15.5 | 5.2 to 25.5
CSF (inflamed) | 20 mg/kg [in pediatric patients of age 5 months to 8 years]; 40 mg/kg [in pediatric patients of age 1 month to 15 years (Meropenem for Injection is not approved for use in pediatric patients younger than 3 months of age)] | 8; 5 | 1.1 (2 hours); 3.3 (3 hours) | 0.2 to 2.8; 0.9 to 6.5
CSF (uninflamed) | 1 | 4 | 0.2 (2 hours) | 0.1 to 0.3

Elimination

In subjects with normal renal function, the elimination half-life of meropenem is approximately 1 hour. The elimination half-life for meropenem was approximately 1.5 hours in pediatric patients 3 months to 2 years of age.

Metabolism

There is one metabolite of meropenem that is microbiologically inactive.

Excretion

Meropenem is primarily excreted unchanged by the kidneys. Approximately 70% (50% to 75%) of the dose is excreted unchanged within 12 hours. A further 28% is recovered as the microbiologically inactive metabolite. Fecal elimination represents only approximately 2% of the dose. The measured renal clearance and the effect of probenecid show that meropenem undergoes both filtration and tubular secretion. Urinary concentrations of meropenem in excess of 10 mcg/mL are maintained for up to 5 hours after a 500 mg dose.

Specific Populations

Patients with Hepatic Impairment

A pharmacokinetic study with meropenem for injection in patients with hepatic impairment has shown no effects of liver disease on the pharmacokinetics of meropenem.

Patients with Renal Impairment

Pharmacokinetic (PK) studies with meopenem for injection in adult patients with renal impairment have shown that the reduction in plasma clearance of meropenem correlates with creatinine clearance. The effect of renal impairment on the PK of meropenem has not been studied in the pediatric patients. Therefore, there is no experience in pediatric patients with renal impairment [see Dosage and Administration (2.3)].

Drug Interaction Studies

Probenecid competes with meropenem for active tubular secretion and thus inhibits the renal excretion of meropenem. Following administration of probenecid with meropenem, the mean systemic exposure increased 56% and the mean elimination half-life increased 38% [see Drug Interactions (7.1)].

12.4 Microbiology

Mechanism of Action

The bactericidal activity of meropenem results from the inhibition of cell wall synthesis. Meropenem penetrates the cell wall of most gram-positive and gram-negative bacteria to bind penicillin-binding-protein (PBP) targets. Meropenem binds to PBPs 2, 3 and 4 of Escherichia coli and Pseudomonas aeruginosa; and PBPs 1, 2 and 4 of Staphylococcus aureus. Bactericidal concentrations (defined as a 3 log10 reduction in cell counts within 12 hours to 24 hours) are typically 1-2 times the bacteriostatic concentrations of meropenem, with the exception of Listeria monocytogenes, against which lethal activity is not observed.

Meropenem does not have in vitro activity against methicillin-resistant Staphylococcus aureus (MRSA) or methicillin-resistant Staphylococcus epidermidis (MRSE).

Resistance

There are several mechanisms of resistance to carbapenems: 1) decreased permeability of the outer membrane of gram-negative bacteria (due to diminished production of porins) causing reduced bacterial uptake, 2) reduced affinity of the target PBPs, 3) increased expression of efflux pump components, and 4) production of antibacterial drug-destroying enzymes (carbapenemases, metallo-β-lactamases).

Cross-resistance is sometimes observed with isolates resistant to other carbapenems.

Interaction with Other Antimicrobials

In vitro tests show meropenem to act synergistically with aminoglycoside antibacterial drugs against some isolates of Pseudomonas aeruginosa.

Antimicrobial Activity

Meropenem has been shown to be active against most isolates of the following microorganisms, both in vitro and in clinical infections [see Indications and Usage (1)].

Gram-positive bacteria

Streptococcus pneumoniae (penicillin-susceptible isolates only)

Gram-negative bacteria

Haemophilus influenzae

Neisseria meningitidis

The following in vitro data are available, but their clinical significance is unknown. At least 90% of the following bacteria exhibit an in vitro minimum inhibitory concentration (MIC) less than or equal to the susceptible breakpoint for meropenem against isolates of similar genus or organism group. However, the efficacy of meropenem in treating clinical infections caused by these bacteria have not been established in adequate and well-controlled clinical trials.

Gram-positive bacteria

Staphylococcus epidermidis (methicillin-susceptible isolates only)

Gram-negative bacteria

Aeromonas hydrophila

Campylobacter jejuni

Citrobacter freundii

Citrobacter koseri

Enterobacter cloacae

Hafnia alvei

Klebsiella oxytoca

Moraxella catarrhalis

Morganella morganii

Pasteurella multocida

Proteus vulgaris

Serratia marcescens

Anaerobic bacteria

Bacteroides ovatus

Bacteroides uniformis

Bacteroides vulgatus

Clostridium difficile

Clostridium perfringens

Eggerthella lenta

Fusobacterium species

Prevotella intermedia

Prevotella melaninogenica

Propionibacterium acnes

Susceptibility Testing

For specific information regarding susceptibility test interpretive criteria and associated test methods and quality control standards recognized by FDA for this drug, please see: https://www.fda.gov/STIC.

13 NONCLINICAL TOXICOLOGY

13.1 Carcinogenesis, Mutagenesis, Impairment of Fertility

Carcinogenesis

Carcinogenesis studies have not been performed.

Mutagenesis

Genetic toxicity studies were performed with meropenem using the bacterial reverse mutation test, the Chinese hamster ovary HGPRT assay, cultured human lymphocytes cytogenic assay, and the mouse micronucleus test. There was no evidence of mutagenic potential found in any of these tests.

Impairment of Fertility

In fertility studies, intravenous meropenem was administered to male rats beginning 11 weeks before mating and throughout mating and to female rats from 2 weeks before mating through Gestation Day 7 at doses of 240, 500, and 1000 mg/kg/day. There was no evidence of impaired fertility at doses up to 1000 mg/kg/day (on the basis of body surface area comparison, approximately 3.2 times to the MRHD of 1 gram every 8 hours).

14 CLINICAL STUDIES

14.1 Bacterial Meningitis

Four hundred forty-six patients (397 pediatric patients 3 months to less than 17 years of age) were enrolled in 4 separate clinical trials and randomized to treatment with meropenem for injection (n = 225) at a dosage of 40 mg/kg every 8 hours or a comparator drug, i.e., cefotaxime (n = 187) or ceftriaxone (n = 34), at the approved dosing regimens. A comparable number of patients were found to be clinically evaluable (ranging from 61 to 68%) and with a similar distribution of pathogens isolated on initial CSF culture.

A patient was defined as clinically not cured if any one of the following three criteria were met:

1 At the 5-7 week post-completion of therapy visit, the patient had any one of the following: moderate to severe motor, behavior or development deficits, hearing loss of greater than 60 decibels in one or both ears, or blindness.
2 During therapy the patient’s clinical status necessitated the addition of other antibacterial drugs.
3 Either during or post-therapy, the patient developed a large subdural effusion needing surgical drainage, or a cerebral abscess, or a bacteriologic relapse.

Using these criteria, the following efficacy rates were obtained, per organism (noted in Table 3). The values represent the number of patients clinically cured/number of clinically evaluable patients, with the percent cure in parentheses. Sequelae were the most common reason patients were assessed as clinically not cured.

Table 3: Efficacy rates by Pathogen in the Clinically Evaluable Population with Bacterial Meningitis

Microorganisms | Meropenem for Injection | Comparator
S. pneumoniae | 17/24 (71) | 19/30 (63)
H. influenzae (+) [(+) β-lactamase-producing] | 8/10 (80) | 6/6 (100)
H. influenzae (-/NT) [(-/NT) non-β-lactamase-producing or not tested] | 44/59 (75) | 44/60 (73)
N. meningitidis | 30/35 (86) | 35/39 (90)
Total (including others) | 102/131 (78) | 108/140 (77)

Five patients were found to be bacteriologically not cured, 3 in the comparator group (1 relapse and 2 patients with cerebral abscesses) and 2 in the meropenem for injection group (1 relapse and 1 with continued growth of Pseudomonas aeruginosa).

With respect to hearing loss, 263 of the 271 evaluable patients had at least one hearing test performed post-therapy. Table 4 shows the degree of hearing loss between the meropenem for injection-treated patients and comparator-treated patients.

Table 4: Hearing Loss at Post-Therapy in the Evaluable Population Treated with Meropenem

Degree of Hearing Loss; (in one or both ears) | Meropenem for Injection; n = 128 | Comparator; n = 135
No loss | 61% | 56%
20 to 40 decibels | 20% | 24%
Greater than 40 to 60 decibels | 8% | 7%
Greater than 60 decibels | 9% | 10%

15 REFERENCES

1. Kawamura S, AW Russell, SJ Freeman, and RA Siddall, 1992, Reproductive and Developmental Toxicity of Meropenem in Rats, Chemotherapy, 40:S238-250.

16 HOW SUPPLIED/STORAGE AND HANDLING

Meropenem for Injection is supplied in a single-dose vial containing meropenem as a white to light yellow powder to deliver 2 grams of meropenem for intravenous administration after reconstitution. The dry powder should be stored at 20º C to 25ºC (68º F to 77ºF). Brief exposure to 15ºC to 30ºC (59ºF to 86ºF) is permitted [see USP Controlled Room Temperature].

NDC 44567-402-01 2 gram single-dose injection vial

NDC 44567-402-06 2 gram single-dose injection vial packaged in a carton of 6

The container closure is not made with natural rubber latex.

17 PATIENT COUNSELING INFORMATION

Antibacterial Resistance

Patients should be counseled that antibacterial drugs including Meropenem for Injection should only be used to treat bacterial infections. They do not treat viral infections (e.g., the common cold). When Meropenem for Injection is prescribed to treat a bacterial infection, patients should be told that although it is common to feel better early in the course of therapy, the medication should be taken exactly as directed. Skipping doses or not completing the full course of therapy may (1) decrease the effectiveness of the immediate treatment and (2) increase the likelihood that bacteria will develop resistance and will not be treatable by Meropenem for Injection or other antibacterial drugs in the future [see Warnings and Precautions (5.7)].

Diarrhea

Counsel patients that diarrhea is a common problem caused by antibacterial drugs which usually ends when the antibacterial drug is discontinued. Sometimes after starting treatment with antibacterial drugs, patients can develop watery and bloody stools (with or without stomach cramps and fever) even as late as two or more months after having taken the last dose of the antibacterial drug. If this occurs, patients should contact their physician as soon as possible [see Warnings and Precautions (5.6)].

Risk of Breakthrough Seizures

Counsel patients to inform their physician if they are taking valproic acid or divalproex sodium. Valproic acid concentrations in the blood may drop below the therapeutic range upon co-administration with Meropenem for Injection. If treatment with Meropenem for Injection is necessary and continued, alternative or supplemental anti-convulsant medication to prevent and/or treat seizures may be needed [see Warnings and Precautions (5.4)].

Potential of Neuromotor Impairment

Patients receiving Meropenem for Injection on an outpatient basis must be alerted of adverse events such as seizures, delirium, headaches and/or paresthesias that could interfere with mental alertness and/or cause motor impairment. Until it is reasonably well established that Meropenem for Injection is well tolerated, patients should not operate machinery or motorized vehicles [see Warnings and Precautions (5.10)].

Manufactured for:

WG Critical Care, LLC

Paramus, NJ 07652

Made in Italy

PRINCIPAL DISPLAY PANEL

NDC 44567-402-01
Meropenem for Injection, USP
2 grams per vial
For Intravenous Infusion Only
Single-Dose Vial – Discard Unused Portion
Rx only